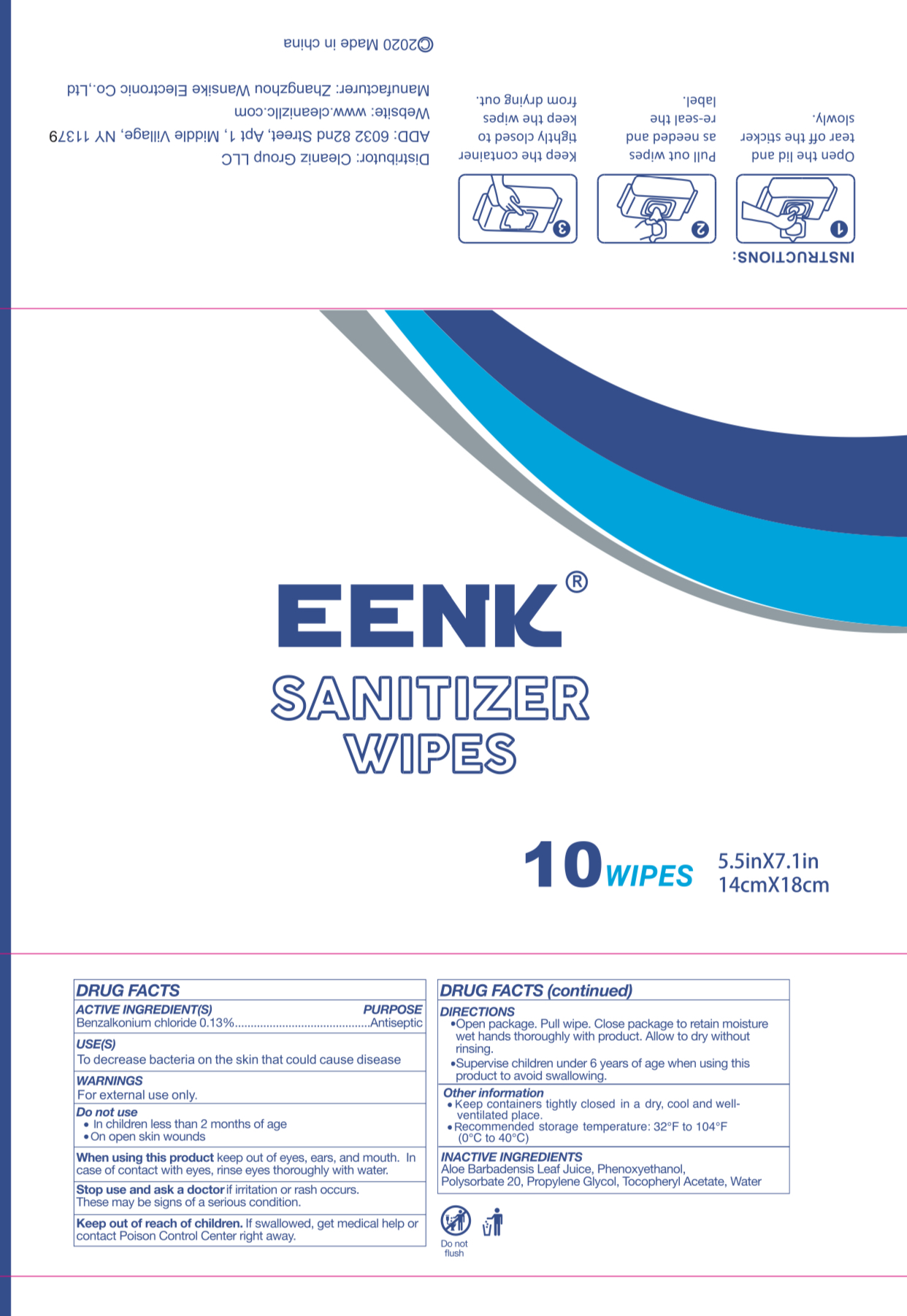 DRUG LABEL: EENK SANITIZER WIPES
NDC: 81635-001 | Form: SOLUTION
Manufacturer: CLEANIZ GROUP LLC
Category: otc | Type: HUMAN OTC DRUG LABEL
Date: 20210313

ACTIVE INGREDIENTS: BENZALKONIUM CHLORIDE 0.13 g/100 mL
INACTIVE INGREDIENTS: PROPYLENE GLYCOL; POLYSORBATE 20; WATER; PHENOXYETHANOL; ALOE VERA LEAF; .ALPHA.-TOCOPHEROL ACETATE

81635-001

Active Ingredient

Benzalkonium Chloride 0.13%

Purpose

Antiseptic

Use

■ To decrease bacteria on the skin that could cause disease

WARNINGS

For external use only

Do not use

In children less than two monthsof age.

On open skin wounds

When using this product, keep out of eyes, ears, and mouth. In case of contact with eyes, rinse thoroughly with water.

Stop use and ask a doctor if irritation or rash occurs. These may be signs of a serious condition

Keep out of reach of children. If swallowed, get medical help or contact a Poison Control Center right away.

Directions

Open package, pull wipe. Close package to retain moisture. Wet hands thoroughly with product. Allow to dry without rinsing

Supervise children under six years of age when using this product to avoid swallowing

Other Information

Keep container tightly closed in a dry, cool, and well ventilated place.

Recommended storage temperature: 32F to 104F (0C to 40C)

Inactive ingredients

Alow Barbadensis leaf jiuce, Phenoxyethanol, Polysorbate 20, Propylene glycol, Tocopheryl Acetate, Water